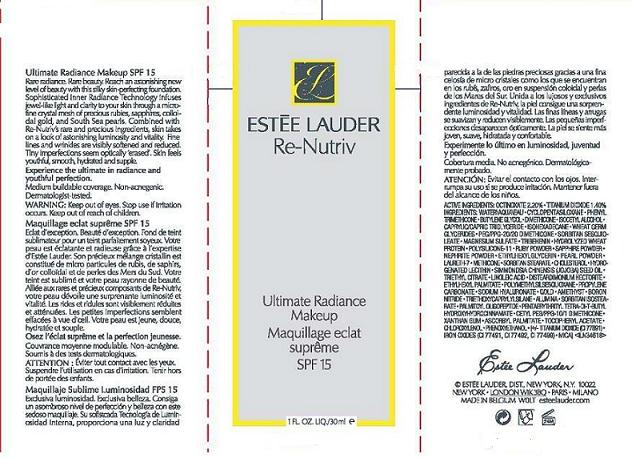 DRUG LABEL: RENUTRIV
NDC: 11559-746 | Form: LIQUID
Manufacturer: ESTEE LAUDER INC
Category: otc | Type: HUMAN OTC DRUG LABEL
Date: 20101202

ACTIVE INGREDIENTS: OCTINOXATE 2.2 mL/100 mL; TITANIUM DIOXIDE 1.4 mL/100 mL
INACTIVE INGREDIENTS: WATER; BUTYLENE GLYCOL; DIMETHICONE

ACTIVE INGREDIENT

ACTIVE INGREDIENTS: OCTINOXATE 2.20% [] TITANIUM DIOXIDE 1.40%

INACTIVE INGREDIENT

INACTIVE INGREDIENTS: WATER\AQUA\EAU [] CYCLOPENTASILOXANE [] PHENYL TRIMETHICONE [] BUTYLENE GLYCOL [] DIMETHICONE [] ISOCETYL ALCOHOL [] CAPRYLIC/CAPRIC TRIGLYCERIDE [] ISOHEXADECANE [] WHEAT GERM GLYCERIDES [] PEG/PPG-20/20 DIMETHICONE [] SORBITAN SESQUIOLEATE [] MAGNESIUM SULFATE [] TRIBEHENIN [] HYDROLYZED WHEAT PROTEIN [] POLYSILICONE-11 [] RUBY POWDER [] SAPPHIRE POWDER [] NEPHRITE POWDER [] ETHYLHEXYLGLYCERIN [] PEARL POWDER [] LAURETH-7 [] METHICONE [] SORBITAN STEARATE [] CHOLESTEROL [] HYDROGENATED LECITHIN [] SIMMONDSIA CHINENSIS (JOJOBA) SEED OIL [] TRIETHYL CITRATE [] LINOLEIC ACID [] DISTEARDIMONIUM HECTORITE [] ETHYLHEXYL PALMITATE [] POLYMETHYLSILSESQUIOXANE [] PROPYLENE CARBONATE [] SODIUM HYALURONATE [] GOLD [] AMETHYST [] BORON NITRIDE [] TRIETHOXYCAPRYLYLSILANE [] ALUMINA [] SORBITAN ISOSTEARATE [] PALMITOYL OLIGOPEPTIDE [] PENTAERYTHRITYL TETRA-DI-T-BUTYL HYDROXYHYDROCINNAMATE [] CETYL PEG/PPG-10/1 DIMETHICONE [] XANTHAN GUM [] ASCORBYL PALMITATE [] TOCOPHERYL ACETATE [] CHLOROXYLENOL [] PHENOXYETHANOL [] [+/- TITANIUM DIOXIDE (CI 77891) [] IRON OXIDES (CI 77491, CI 77492, CI 77499) [] MICA

WARNINGS

WARNING: KEEP OUT OF EYES. STOP USE IF IRRITATION OCCURS.

KEEP OUT OF REACH OF CHILDREN.

PACKAGE LABEL

PRINCIPAL DISPLAY PANEL

ESTEE LAUDER

RE-NUTRIV

ULTIMATE RADIANCE MAKEUP

SPF 15

1 FL OZ LIQUID/30 ML

ESTEE LAUDER DISTR.

NY, NY 10022